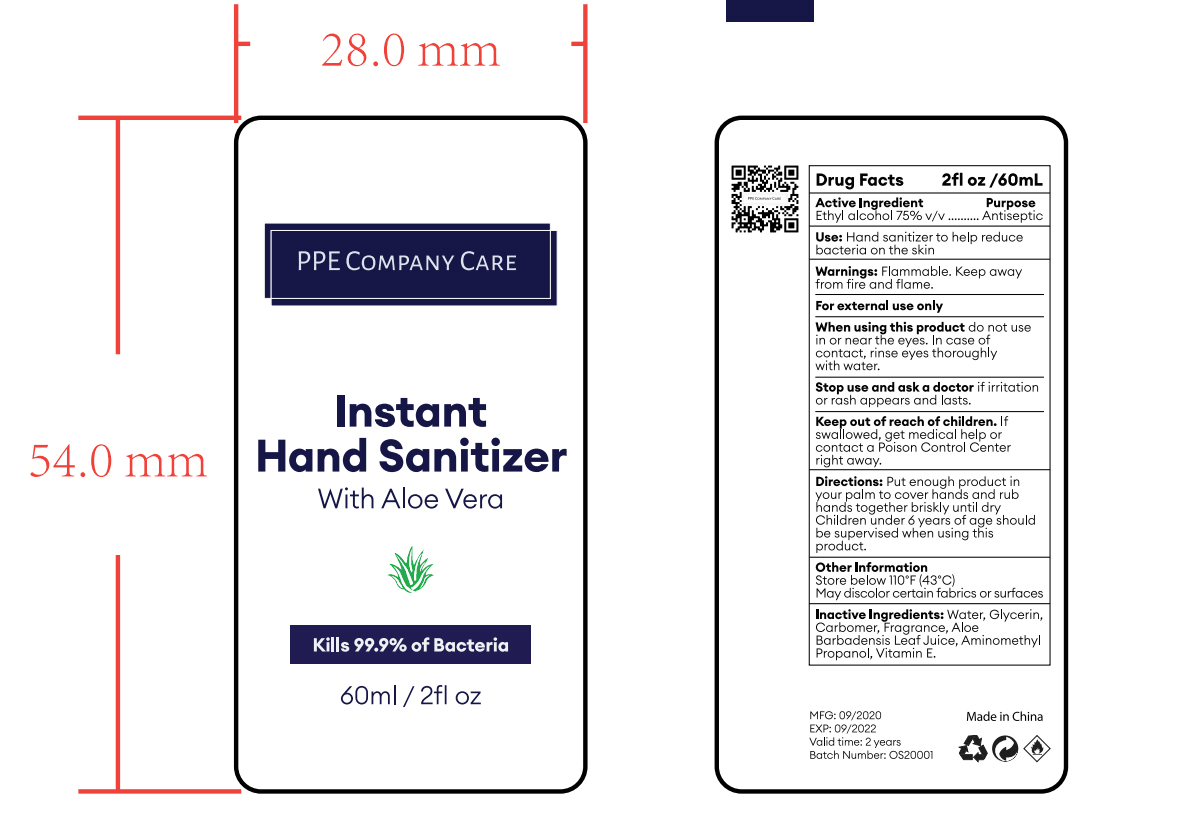 DRUG LABEL: HAND SANITIZER
NDC: 47993-319 | Form: GEL
Manufacturer: NINGBO JIANGBEI OCEAN STAR TRADING CO.,LTD
Category: otc | Type: HUMAN OTC DRUG LABEL
Date: 20201102

ACTIVE INGREDIENTS: ALCOHOL 75 mL/100 mL
INACTIVE INGREDIENTS: WATER; GLYCERIN; CARBOMER 940; ALOE VERA LEAF; AMINOMETHYLPROPANOL; TOCOPHEROL

47993-319

Active Ingredients

Ethyl alcohol 75% v/v

PURPOSE

Antiseptic

Uses：

Hand sanitizer to help reduce bactria on the skin.

Warnings:

Flammable. Keep away from fire and flame.

For external use only.

When using this product do not use in or near the eyes. In case of contact, rinse eyes thoroughly with water.

Stop use and ask a doctor if irritation or rash appears and lasts.

Keep out of reach of children. If swallowed，get medical help or contact a Poison Control Center right away.

Directions:

Put enough product in your palm to cover hands and rub hands together briskly until dry Children under 6 years of age should be supervised when using this product.

Other Information

Store below 110℉(43℃).

May discolor certain fabrics or surface.

Inactive Ingredients:

Water, Glycerin, Carbomer, Fragrance, Aloe Barbadensis Leaf Juice, Aminomethyl Propanol, Vitamin E.